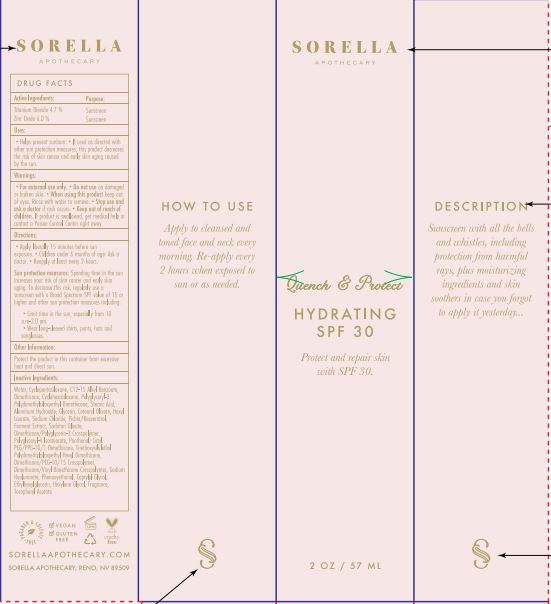 DRUG LABEL: Quench and Protect Hydrating SPF30
NDC: 62742-4230 | Form: CREAM
Manufacturer: Allure Labs.
Category: otc | Type: HUMAN OTC DRUG LABEL
Date: 20241209

ACTIVE INGREDIENTS: ZINC OXIDE 6 g/100 g; TITANIUM DIOXIDE 4.7 g/100 g
INACTIVE INGREDIENTS: ETHYLHEXYLGLYCERIN; WATER; ALUMINUM HYDROXIDE; PRUNUS PERSICA SEED; STEARIC ACID; DIMETHICONE; CYCLOMETHICONE 6; POLYGLYCERYL-3 POLYDIMETHYLSILOXYETHYL DIMETHICONE (4000 MPA.S); GLYCERIN; HEXYL LAURATE; RESVERATROL; CETYL PEG/PPG-10/1 DIMETHICONE (HLB 4); CETEARYL OLIVATE; SODIUM CHLORIDE; CAPRYLYL GLYCOL; POLYGLYCERYL-4 ISOSTEARATE; PANTHENOL; TRIETHOXYSILYLETHYL POLYDIMETHYLSILOXYETHYL HEXYL DIMETHICONE; DIMETHICONE/PEG-10/15 CROSSPOLYMER; HYALURONATE SODIUM; HEXYLENE GLYCOL; SORBITAN OLIVATE; ALKYL (C12-15) BENZOATE; .ALPHA.-TOCOPHEROL ACETATE; CYCLOMETHICONE 7; DIMETHICONE/POLYGLYCERIN-3 CROSSPOLYMER; PHENOXYETHANOL

Drug Facts

ACTIVE INGREDIENTS:
Zinc Oxide - 6.0%
Titanium Dioxide 4.7%

Purpose: Sunscreen

INDICATIONS AND USAGE

Uses: Helps prevent sunburn. If used as directed with other sun protection measures, this product decreases the risk of skin cancer and early skin aging caused by the sun.

Warning:

For external use only

Do not use on damage or broken skin.

When using this product keep out of eye. Rinse with water to remove.

Stop use and ask a doctor if rash occurs.

Keep out of reach of children if product is swallowed, get medical help or contact a poison control center right away.

DOSAGE AND ADMINISTRATION

Direction:

Apply liberally 15 minutes before sun exposure.

Children under 6 month of age: Ask a doctor

Reapply at least every 2 hours.

Sun protection measures: Spending time in the sun increases your risk of skin cancer and early skin aging. To decreases this risk regularly use a sunscreen with a broad spectrum SPF value of 15 or higher and other sun protection measures including: Limit time in the sun< especially from 10 am – 2.0 pm, Wear long – sleeved shirts, pants, hats and sunglasses.

Other Information:

Protect the product in this container from excessive heat and direct sun.

INACTIVE INGREDIENT: Water, Cyclopentasiloxane, C12-15 Alkyl Benzoate, Dimethicone, Cyclohexasiloxane, Polyglyceryl-3 Polydimethylsiloxyethyl Dimethicone, Aluminum Hydroxide, Stearic Acid, Glycerin, Cetearyl Olivate,Hexyl Laurate, Sodium Chloride, Pichia/ Resveratrol, Ferment Extract, Sorbitane Olivate, Dimethicone/Polyglycerin -3 Crosspolymer, Polyglyceryl-4 Isostearate, Panthenol, Cetyl PEG/PPG-10/1 Dimethicone, Triethoxysilylethyl Polydimethylsiloxyethyl HexylDimethicone, Dimethicone/PEG-10/15 Crosspolymer, Dimethicone/Venyl Dimethicone, Crosspolymer, Sodium Hyaluronate, Phenoxyethanol, Caprylyl Glycol, Ethylhexylglycerin, Hexylene Glycol, Fragrance, Tocopheryl Acetate.